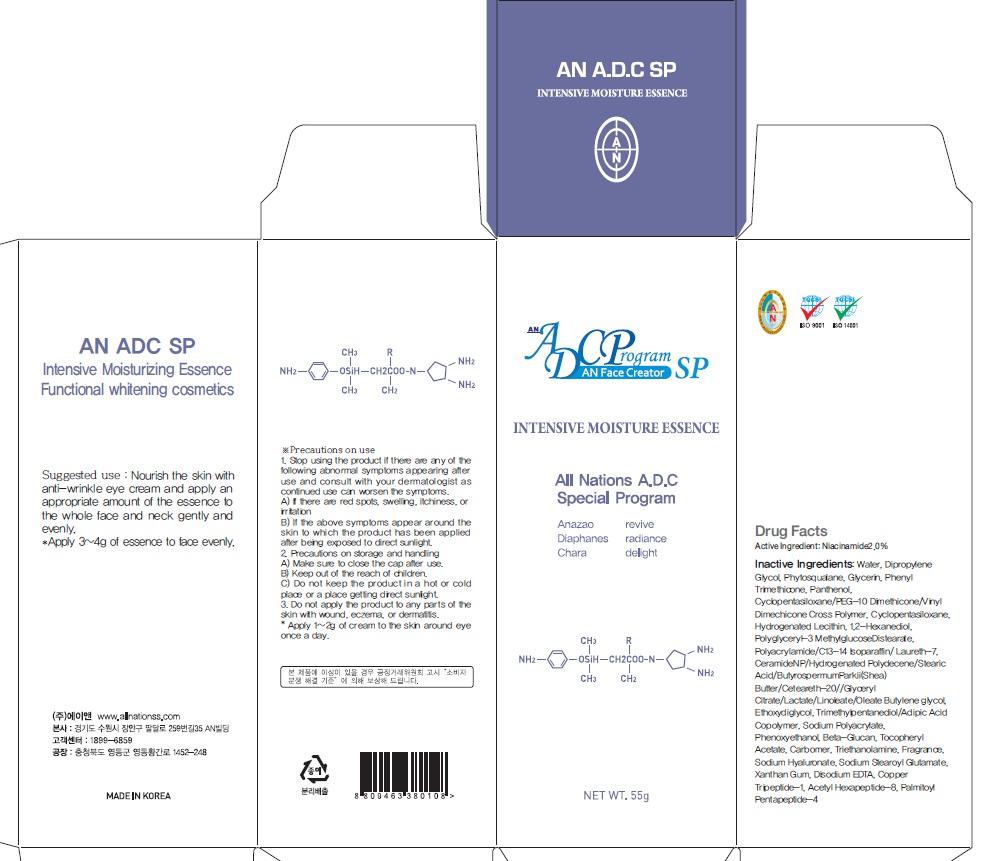 DRUG LABEL: AN ADC SP INTENSIVE MOISTURE ESSENCE
NDC: 69153-080 | Form: CREAM
Manufacturer: AN Co Ltd.
Category: otc | Type: HUMAN OTC DRUG LABEL
Date: 20160624

ACTIVE INGREDIENTS: Niacinamide 1.10 g/55 g
INACTIVE INGREDIENTS: Water; Dipropylene Glycol

ACTIVE INGREDIENT

Active Ingredient: Niacinamide 2.0%

INACTIVE INGREDIENT

Inactive Ingredients: Water, Dipropylene Glycol, Phytosqualane, Glycerin, Phenyl Trimethicone, Panthenol, Cyclopentasiloxane/PEG-10 Dimethicone/Vinyl Dimechicone Cross Polymer, Cyclopentasiloxane, Hydrogenated Lecithin, 1,2-Hexanediol, Polyglyceryl-3 Methylglucose Distearate, Polyacrylamide/C13-14 Isoparaffin/ Laureth-7, CeramideNP/Hydrogenated Polydecene/Stearic Acid/ButyrospermumParkii(Shea) Butter/Ceteareth-20//Glyceryl Citrate/Lactate/Linoleate/Oleate Butylene glycol, Ethoxydiglycol, Trimethylpentanediol/Adipic Acid Copolymer, Sodium Polyacrylate, Phenoxyethanol, Beta-Glucan, Tocopheryl Acetate, Carbomer, Triethanolamine, Fragrance, Sodium Hyaluronate, Sodium Stearoyl Glutamate, Xanthan Gum, Disodium EDTA, Copper Tripeptide-1, Acetyl Hexapeptide-8, Palmitoyl Pentapeptide-4

PURPOSE

Purpose: Skin Protectant

WARNINGS

Precautions on use: 1. Stop using the product if there are any of the following abnormal symptoms appearing after use and consult with your dermatologist as continued use can worsen the symptoms. A) If there are red spots, swelling, itchiness, or irritation B) If the above symptoms appear around the skin to which the product has been applied after being exposed to direct sunlight. 2. Precautions on storage and handling A) Make sure to close the cap after use. B) Keep out of the reach of children. C) Do not keep the product in a hot or cold place or a place getting direct sunlight. 3. Do not apply the product to any parts of the skin with wound, eczema, or dermatitis.

KEEP OUT OF REACH OF CHILDREN

Suggested use

Suggested use: Nourish the skin with anti-wrinkle eye cream and apply an appropriate amount of the essence to the whole face and neck gently and evenly.

DOSAGE & ADMINISTRATION

Dosage & administration: Apply 3~4g of essence to face evenly.